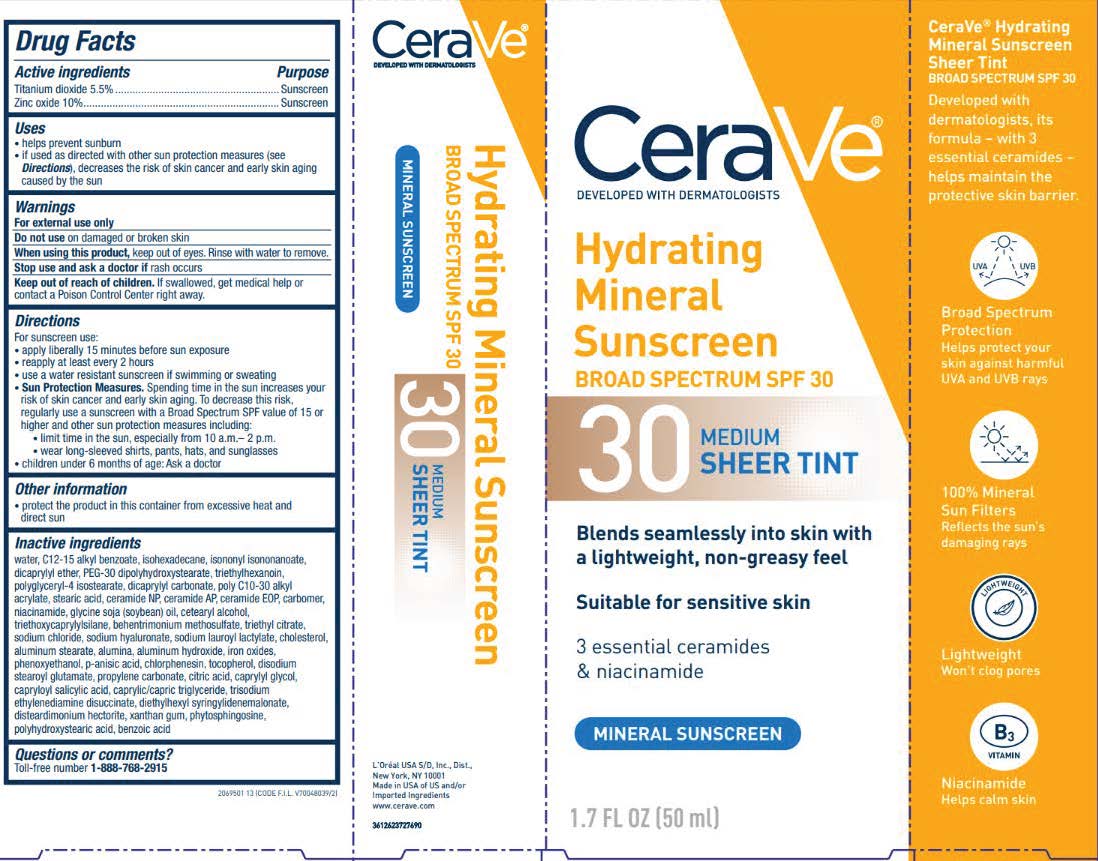 DRUG LABEL: CeraVe Developed with Dermatologists Hydrating Mineral Sunscreen Broad Spectrum SPF 30 Face Sheer Tint Sunscreen
NDC: 49967-231 | Form: LOTION
Manufacturer: L'Oreal USA Products, Inc.
Category: otc | Type: HUMAN OTC DRUG LABEL
Date: 20241219

ACTIVE INGREDIENTS: TITANIUM DIOXIDE 55 mg/1 mL; ZINC OXIDE 100 mg/1 mL
INACTIVE INGREDIENTS: WATER; ALKYL (C12-15) BENZOATE; ISOHEXADECANE; ISONONYL ISONONANOATE; DICAPRYLYL ETHER; PEG-30 DIPOLYHYDROXYSTEARATE; TRIETHYLHEXANOIN; POLYGLYCERYL-4 ISOSTEARATE; DICAPRYLYL CARBONATE; ACRYLIC ACID/ETHYLENE COPOLYMER (600 MPA.S); STEARIC ACID; CERAMIDE NP; CERAMIDE AP; CERAMIDE 1; CARBOMER HOMOPOLYMER TYPE B (ALLYL SUCROSE CROSSLINKED); NIACINAMIDE; GLYCINE SOJA (SOYBEAN) OIL; CETOSTEARYL ALCOHOL; TRIETHOXYCAPRYLYLSILANE; BEHENTRIMONIUM METHOSULFATE; TRIETHYL CITRATE; SODIUM CHLORIDE; HYALURONATE SODIUM; SODIUM LAUROYL LACTYLATE; CHOLESTEROL; ALUMINUM STEARATE; ALUMINUM OXIDE; ALUMINUM HYDROXIDE; FERRIC OXIDE RED; PHENOXYETHANOL; P-ANISIC ACID; CHLORPHENESIN; TOCOPHEROL; EDETATE DISODIUM; DISODIUM STEAROYL GLUTAMATE; PROPYLENE CARBONATE; CITRIC ACID MONOHYDRATE; CAPRYLYL GLYCOL; CAPRYLOYL SALICYLIC ACID; MEDIUM-CHAIN TRIGLYCERIDES; TRISODIUM ETHYLENEDIAMINE DISUCCINATE; DIETHYLHEXYL SYRINGYLIDENEMALONATE; DISTEARDIMONIUM HECTORITE; XANTHAN GUM; PHYTOSPHINGOSINE; POLYHYDROXYSTEARIC ACID (2300 MW); BENZOIC ACID

Drug Facts

Active ingredients

Titanium dioxide 5.5%

Zinc oxide 10%

Purpose

Sunscreen

Uses

• helps prevent sunburn
• if used as directed with other sun protection measures (see Directions), decreases the risk of skin cancer and early skin aging caused by the sun

Warnings

For external use only

Do not use

on damaged or broken skin

When using this product

keep out of eyes. Rinse with water to remove.

Stop use and ask a doctor if

rash occurs

Keep out of reach of children.

If swallowed, get medical help or contact a Poison Control Center right away.

Directions

For sunscreen use:
● apply liberally 15 minutes before sun exposure
● reapply at least every 2 hours
● use a water resistant sunscreen if swimming or sweating
● Sun Protection Measures. Spending time in the sun increases your risk of skin cancer and early skin aging. To decrease this risk, regularly use a sunscreen with a Broad Spectrum SPF value of 15 or higher and other sun protection measures including:
● limit time in the sun, especially from 10 a.m. – 2 p.m.
● wear long-sleeved shirts, pants, hats, and sunglasses
● children under 6 months of age: Ask a doctor

Inactive ingredients

water, c12-15 alkyl benzoate, isohexadecane, isononyl isononanoate, dicaprylyl ether, PEG-30 dipolyhydroxystearate, triethylhexanoin, polyglyceryl-4 isostearate, dicaprylyl carbonate, poly c10-30 alkyl acrylate, stearic acid, ceramide NP, ceramide AP, ceramide EOP, carbomer, niacinamide, glycine soja oil, cetearyl alcohol, triethoxycaprylylsilane, behentrimonium methosulfate, triethyl citrate, sodium chloride, sodium hyaluronate, sodium lauroyl lactylate, cholesterol, aluminum stearate, alumina, aluminum hydroxide, phenoxyethanol, p-anisic acid, chlorphenesin, tocopherol, disodium stearoyl glutamate, propylene carbonate, citric acid, caprylyl glycol, capryloyl salicylic acid, caprylic/capric triglyceride, trisodium ethylenediamine disuccinate, diethylhexyl syringylidenemalonate, disteardimonium hectorite, xanthan gum, phytosphingosine, polyhydroxystearic acid, benzoic acid

Other information

protect the product in this container from excessive heat and direct sun

Questions or comments?

Toll-free number 1-888-768-2915

www.CeraVe.com